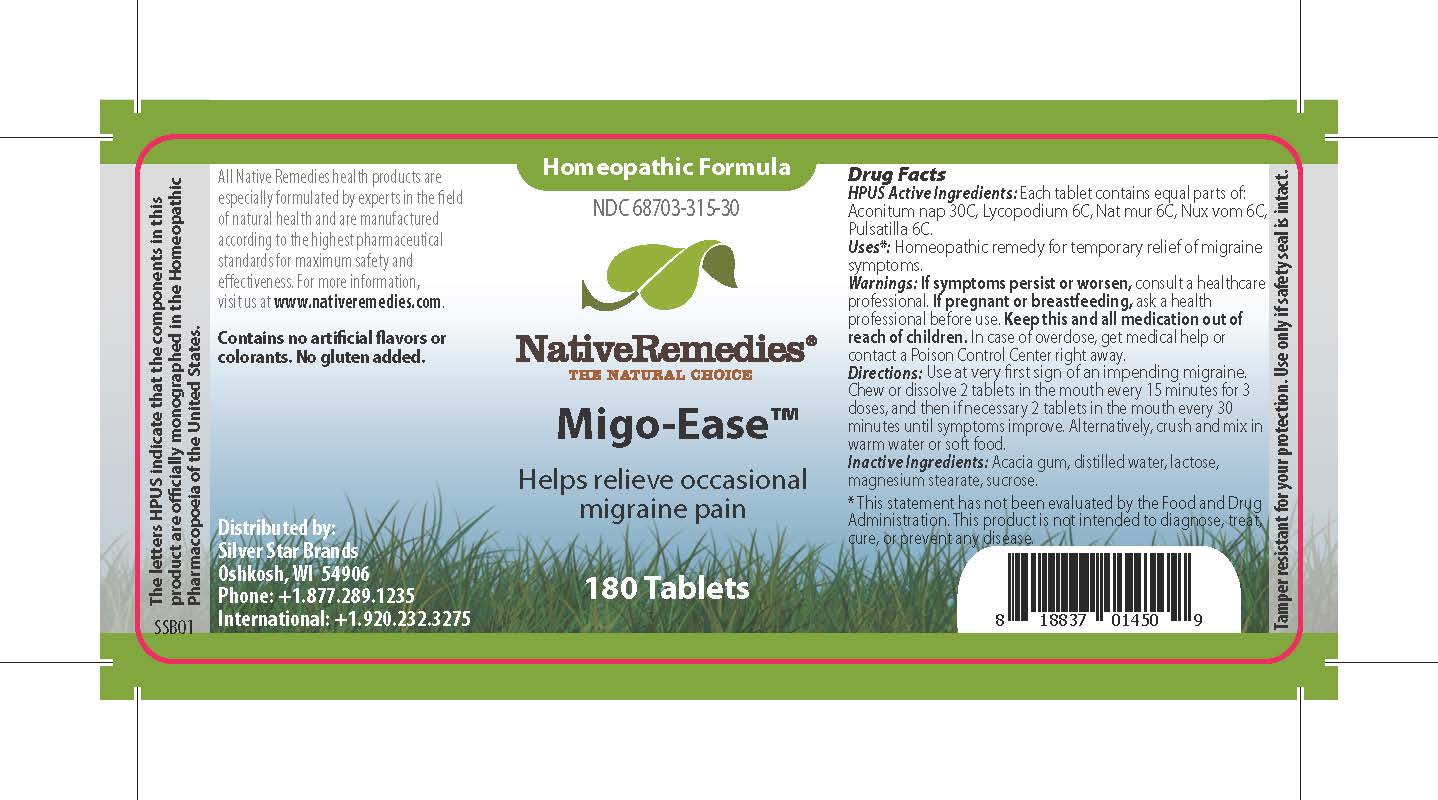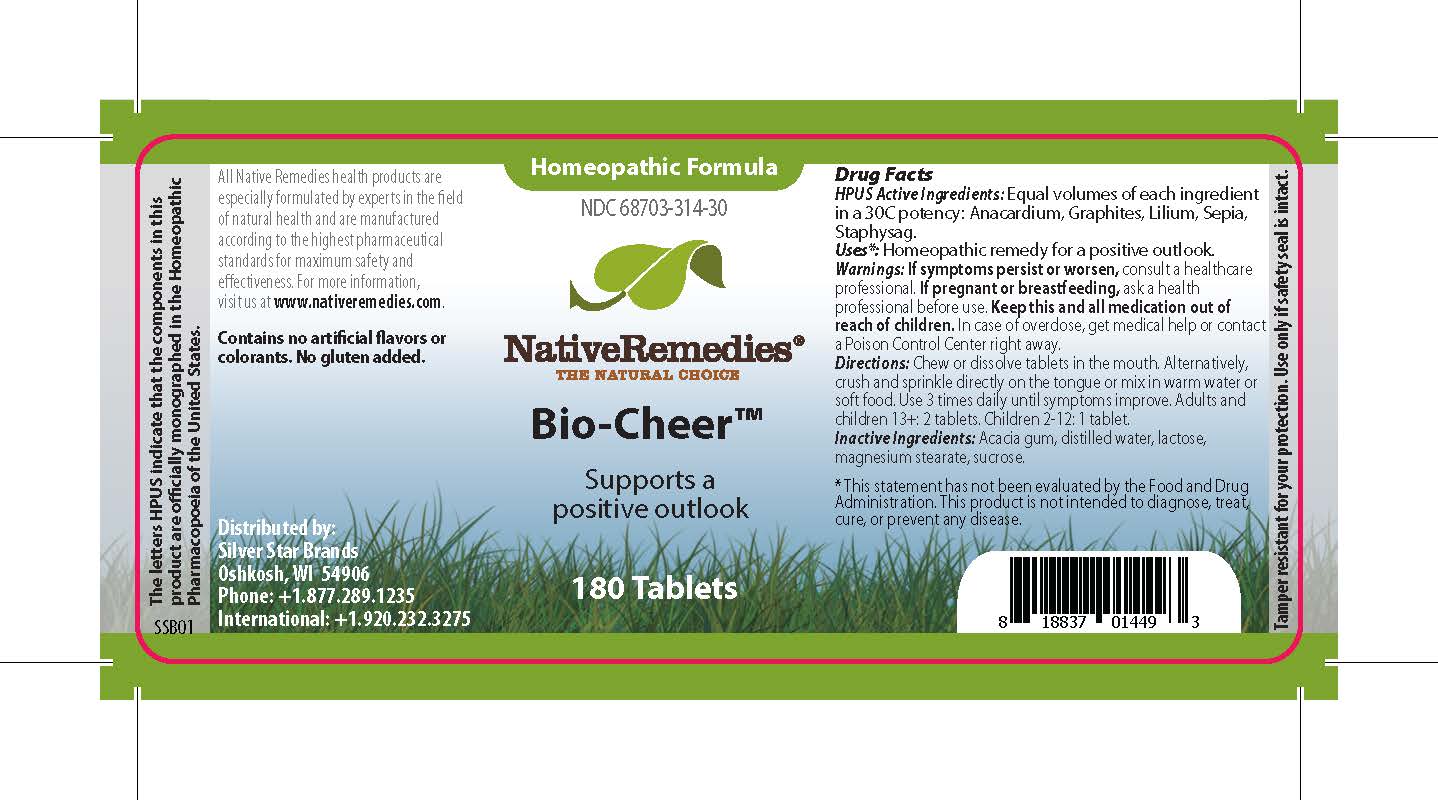 DRUG LABEL: Migo-Ease
NDC: 68703-315 | Form: TABLET
Manufacturer: Silver Star Brands
Category: homeopathic | Type: HUMAN OTC DRUG LABEL
Date: 20241203

ACTIVE INGREDIENTS: LYCOPODIUM CLAVATUM SPORE 6 [hp_C]/1 1; SODIUM CHLORIDE 6 [hp_C]/1 1; PULSATILLA VULGARIS 6 [hp_C]/1 1; STRYCHNOS NUX-VOMICA SEED 6 [hp_C]/1 1; ACONITUM NAPELLUS 30 [hp_C]/1 1
INACTIVE INGREDIENTS: LACTOSE, UNSPECIFIED FORM; SUCROSE; MAGNESIUM STEARATE; WATER; ACACIA

NativeRemedies® Migo-Ease™

HPUS Active Ingredients: Each tablet contains equal parts of: Aconitum nap 30C, Lycopodium 6C, Nat mur 6C, Nux vom 6C, Pulsatilla 6C.

The letters HPUS indicate that the components in this product are officially monographed in the Homeopathic Pharmacopoeia of the United States.

Uses*

Uses*: Homeopathic remedy for temporary relief of migraine symtoms.

*This statement has not been evaluated by the Food and Drug Administration. This product is not intended to diagnose, treat, cure, or prevent any disease.

Warnings

Warnings: If symptoms persist or worsen, consult a healthcare professional. If pregnant or breastfeeding, ask a health professional before use. Keep this and all medications out of reach of children. In case of overdose, get medical help or contact a Poison Control Center right away.

DOSAGE AND ADMINISTRATION

Directions; Use at very first sign of an impending migraine. Chew or dissolve 2 tablets in the mouth every 15 minutes for 3 doses, and then if necessary 2 tablets in the mouth every 30 minutes until symptoms improve. Alternatively, crush and mix in warm water or soft food.

OTHER SAFETY INFORMATION

Contains no artificial flavors or colorants. No gluten added.

Tamper resistant for your protection. Use only if safety seal is intact.

Inactive Ingredients

inactive Ingredients: Acacia gum, distilled water, lactose, magnesium stearate, sucrose.

KEEP OUT OF REACH OF CHILDREN

Keep this and all medication out of reach of children.

PREGNANCY OR BREAST FEEDING

If pregnant or breastfeeding, ask a health professional before use.

PURPOSE

Helps relieve occasional migraine pain.